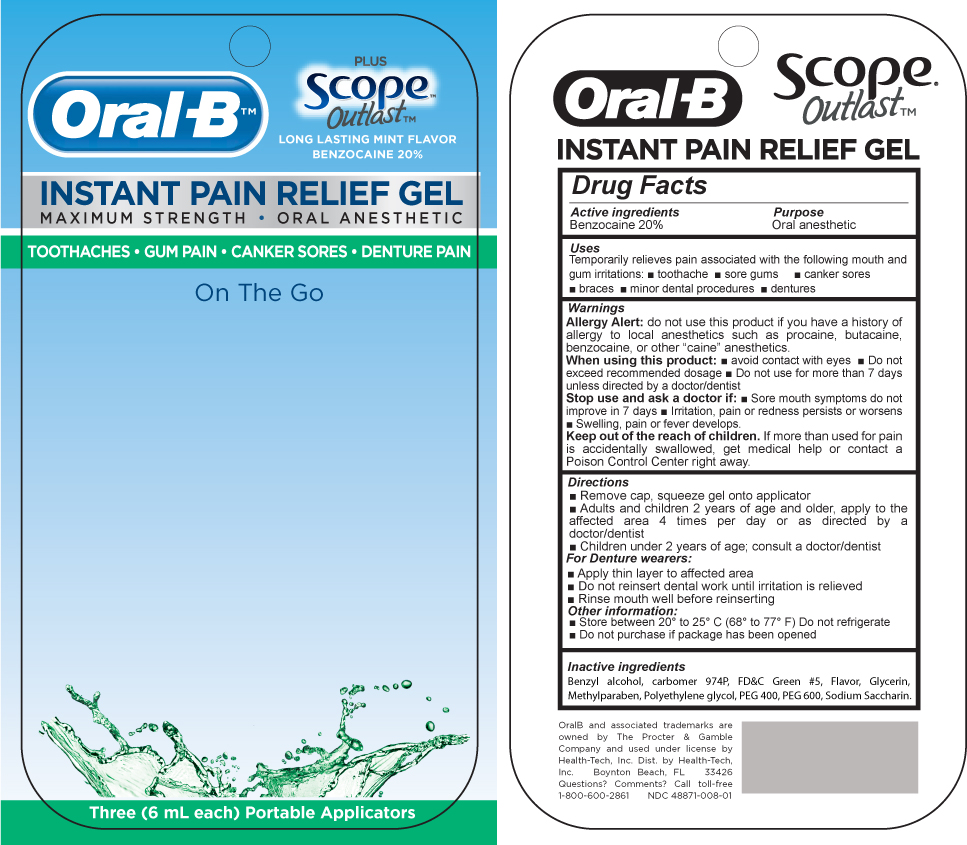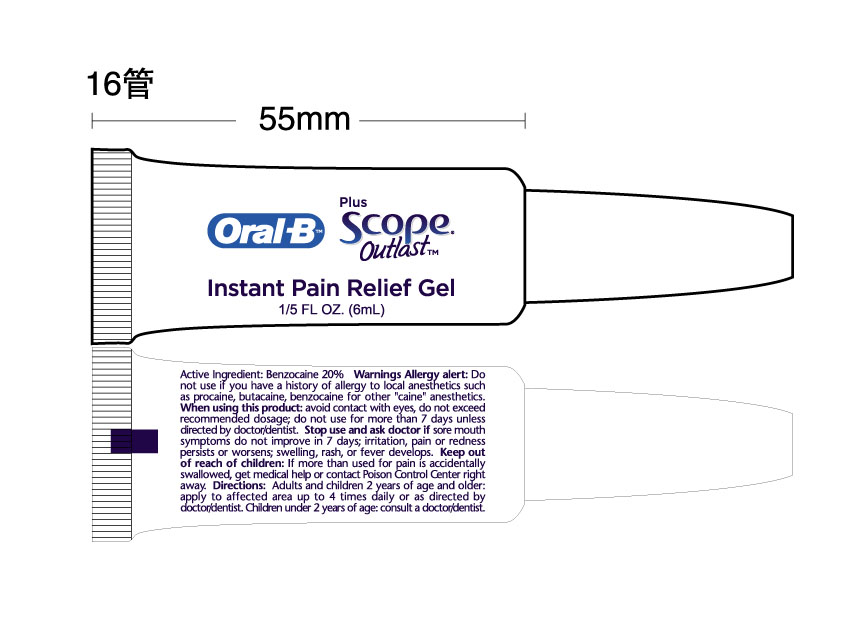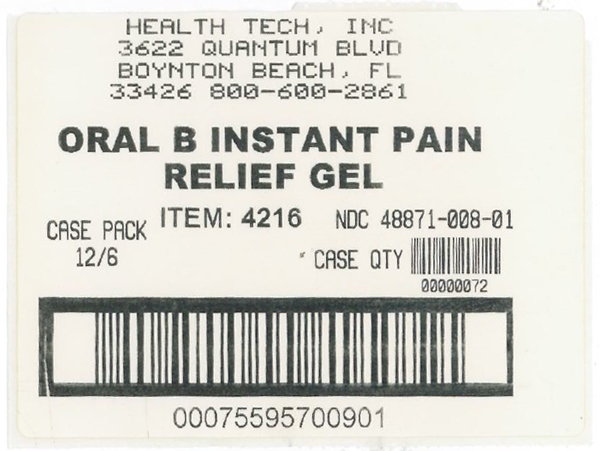 DRUG LABEL: Oral B Instant Pain Relief 
NDC: 48871-008 | Form: GEL
Manufacturer: Health-Tech, Inc.
Category: otc | Type: HUMAN OTC DRUG LABEL
Date: 20100528

ACTIVE INGREDIENTS: Benzocaine 0.2 mL/1 mL
INACTIVE INGREDIENTS: benzyl alcohol; Glycerin; methylparaben; Polyethylene glycol; Polyethylene glycol 400; Polyethylene Glycol 600; Saccharin Sodium; CARBOMER HOMOPOLYMER TYPE B (ALLYL PENTAERYTHRITOL CROSSLINKED)

Drug Facts

Active Ingredient

Benzocaine 20%

Purpose

Oral anesthetic

Uses

Temporarily relieves pain associated with the following mouth and gum irritations:

- toothache
- sore gums
- canker sores
- braces
- minor dental procedures
- dentures

Warnings

Allergy Alert: do not use this pr9oduct if you have a history of allergy to local anesthetics such as procaine, butacaine, benzocaine, or other :caine" anesthetics.

When using this product

- Avoid contact with eyes
- Do not exceed recommended dosage
- Do not use for more than 7 days unless directed by a doctor/dentist

Stop use and ask a doctor if:

- sore mouth symptoms do not improve in 7 days
- Irritation, pain or redness persist or worsens
- Swelling, pain or fever develops

Directions:

- Remove cap-, squeeze gel onto applicator
- Adults and children 2 years of age and older, apply to the affected area 4 times per day or as directed by a doctor/dentist
- Children under 2 years of age; consult a doctor/dentist

For Denture wearers

- Remove Dentures
- Apply thin layer to affected area
- Do not reinsert dental work until irritation is relieved
- Rinse mouth well before reinserting dentures

Other information:

- Store between 20^0 to 25^0 C (68^0 to 77^0 F) Do not refrigerate
- Do not purcahse if package has been opened

Inactive Ingredients

Benzyl alcohol, carbomer 974P, FD and C green 5, Flavor, glycerin, Methylparaben, Polyethylene glycol, PEG 400, PEG 600, Sodium Saccharin

Oral B Pain gel label

MM27

Oral B pain gel blister

MM28

Oral B shipper label

MM29